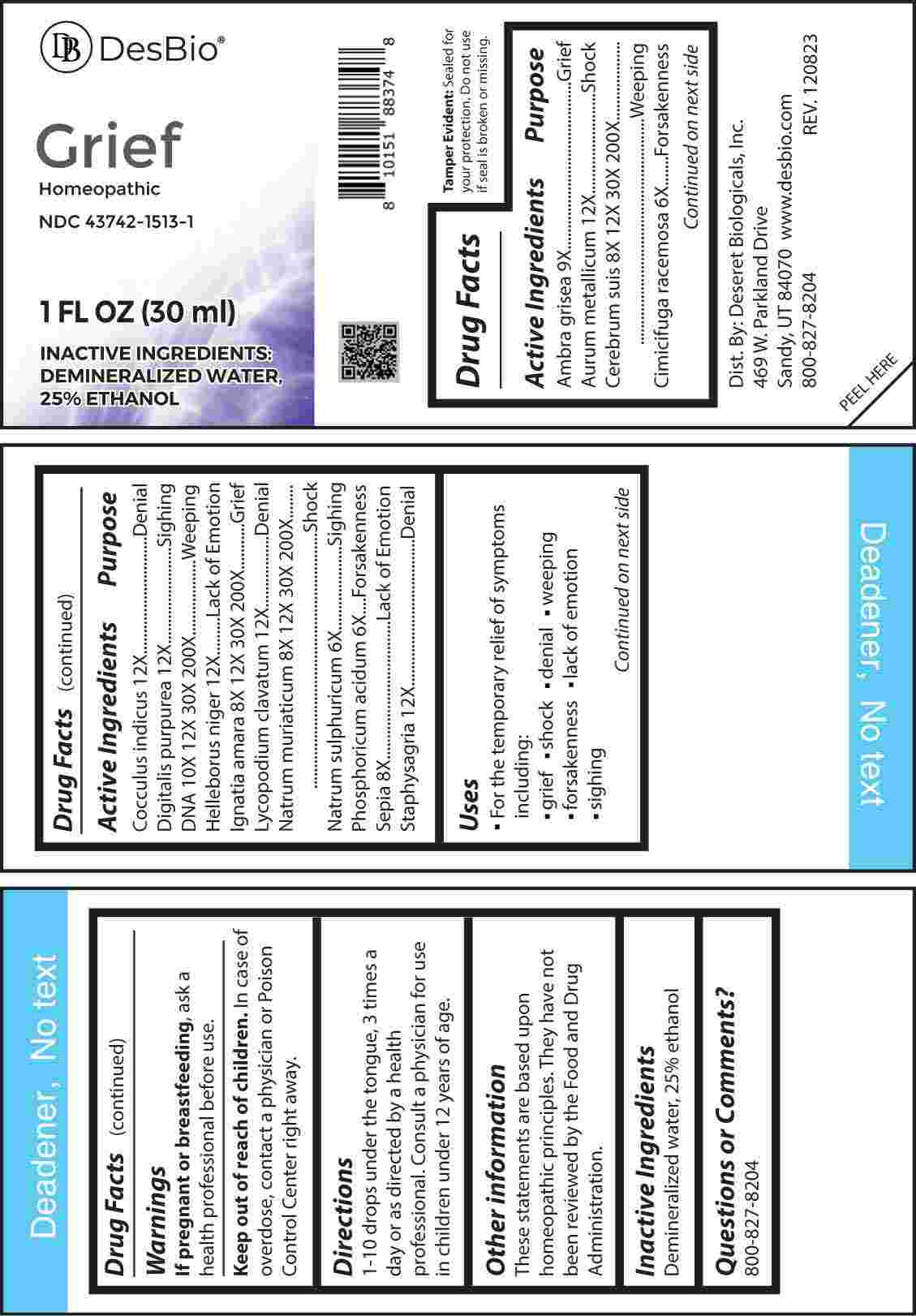 DRUG LABEL: Grief
NDC: 43742-1513 | Form: LIQUID
Manufacturer: Deseret Biologicals, Inc.
Category: homeopathic | Type: HUMAN OTC DRUG LABEL
Date: 20240325

ACTIVE INGREDIENTS: BLACK COHOSH 6 [hp_X]/1 mL; SODIUM SULFATE 6 [hp_X]/1 mL; PHOSPHORIC ACID 6 [hp_X]/1 mL; SEPIA OFFICINALIS JUICE 8 [hp_X]/1 mL; SUS SCROFA CEREBRUM 8 [hp_X]/1 mL; STRYCHNOS IGNATII SEED 8 [hp_X]/1 mL; SODIUM CHLORIDE 8 [hp_X]/1 mL; AMBERGRIS 9 [hp_X]/1 mL; HERRING SPERM DNA 10 [hp_X]/1 mL; GOLD 12 [hp_X]/1 mL; ANAMIRTA COCCULUS SEED 12 [hp_X]/1 mL; DIGITALIS 12 [hp_X]/1 mL; HELLEBORUS NIGER ROOT 12 [hp_X]/1 mL; LYCOPODIUM CLAVATUM SPORE 12 [hp_X]/1 mL; DELPHINIUM STAPHISAGRIA SEED 12 [hp_X]/1 mL
INACTIVE INGREDIENTS: WATER; ALCOHOL

DRUG FACTS:

ACTIVE INGREDIENTS:

Ambra Grisea 9X, Aurum Metallicum 12X, Cerebrum Suis 8X, 12X, 30X, 200X, Cimicifuga Racemosa 6X, Cocculus Indicus 12X, Digitalis Purpurea 12X, DNA 10X, 12X, 30X, 200X, Helleborus Niger 12X, Ignatia Amara 8X, 12X, 30X, 200X, Lycopodium Clavatum 12X, Natrum Muriaticum 8X, 12X, 30X, 200X, Natrum Sulphuricum 6X, Phosphoricum Acidum 6X, Sepia 8X, Staphysagria 12X.

PURPOSE:

Ambra Grisea - Grief, Aurum Metallicum - Shock, Cerebrum Suis - Weeping, Cimicifuga Racemosa - Forsakenness, Cocculus Indicus - Denial, Digitalis Purpurea - Sighing, DNA - Weeping, Helleborus Niger – Lack of Emotion, Ignatia Amara - Grief, Lycopodium Clavatum - Denial, Natrum Muriaticum - Shock, Natrum Sulphuricum - Sighing, Phosphoricum Acidum - Forsakenness, Sepia – Lack of Emotion, Staphysagria - Denial

USES:

• For the temporary relief of symptoms including:

• grief • shock • denial • weeping • forsakenness • lack of emotion • sighing

These statements are based upon homeopathic principles. They have not been reviewed by the Food and Drug Administration.

WARNINGS:

If pregnant or breast-feeding, ask a health professional before use.

Keep out of reach of children. In case of overdose, contact a physician or Poison Control Center right away.

Tamper Evident: Sealed for your protection. Do not use if seal is broken or missing.

KEEP OUT OF REACH OF CHILDREN:

In case of overdose, contact a physician or Poison Control Center right away.

DIRECTIONS:

1-10 drops under the tongue, 3 times a day or as directed by a health professional. Consult a physician for use in children under 12 years of age.

INACTIVE INGREDIENTS:

Demineralized water, 25% ethanol

QUESTIONS:

Dist. By: Deseret Biologicals, Inc.
469 W. Parkland Drive
Sandy, UT 84070

www.desbio.com

800-827-8204

PACKAGE LABEL DISPLAY:

Des Bio

Grief

Homeopathic

NDC 43742-1513-1

1 FL OZ (30 ml)